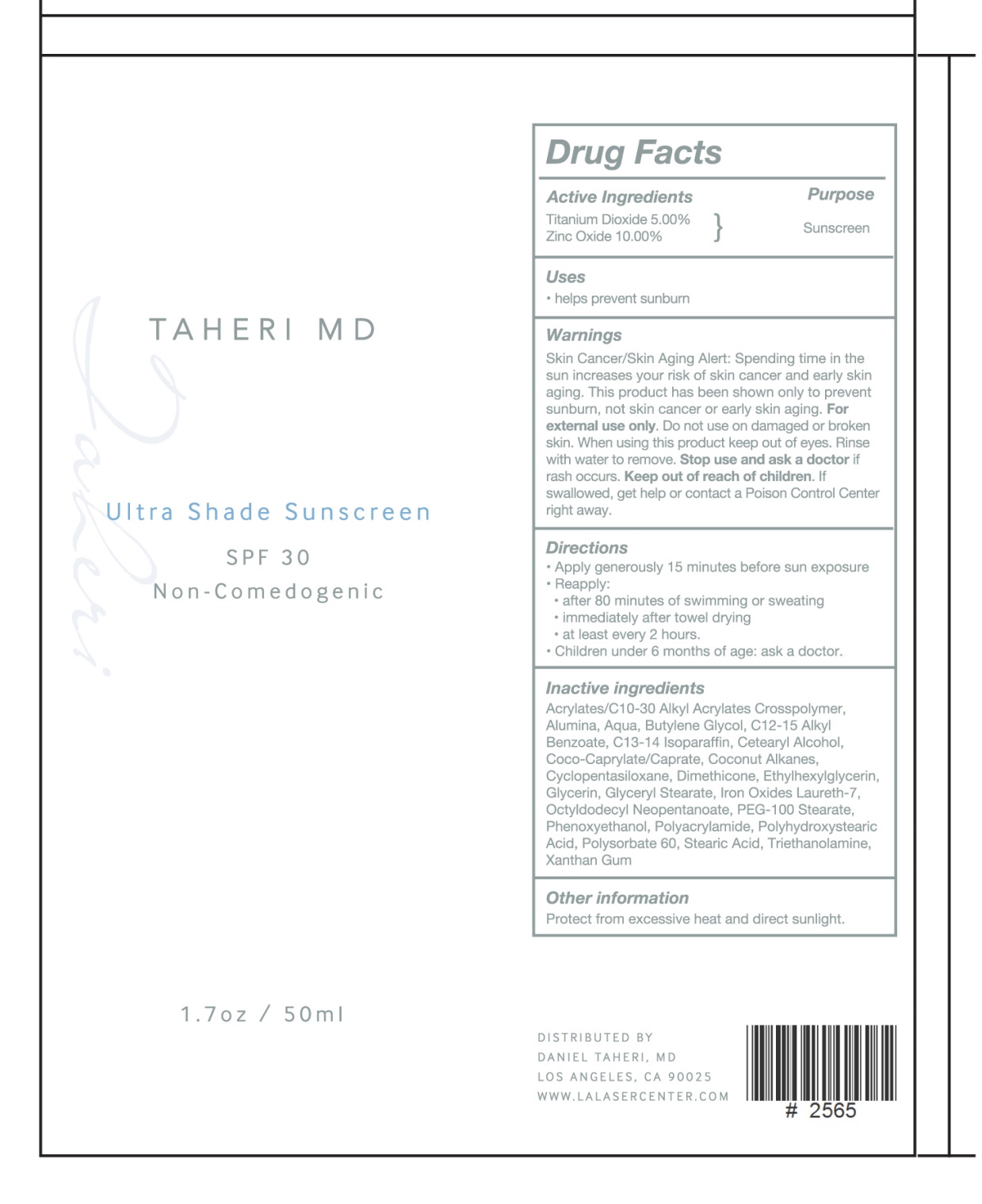 DRUG LABEL: Ultra Shade Sunscreen SPF 30
NDC: 70919-001 | Form: CREAM
Manufacturer: LA LASER CENTE, PC, CALIFORNIA PROFESSIONAL MEDICAL CORP
Category: otc | Type: HUMAN OTC DRUG LABEL
Date: 20170103

ACTIVE INGREDIENTS: TITANIUM DIOXIDE 5 g/100 mL; ZINC OXIDE 10 g/100 mL
INACTIVE INGREDIENTS: CARBOMER INTERPOLYMER TYPE A (ALLYL SUCROSE CROSSLINKED); ALUMINUM OXIDE; WATER; BUTYLENE GLYCOL; ALKYL (C12-15) BENZOATE; C13-14 ISOPARAFFIN; CETOSTEARYL ALCOHOL; COCO-CAPRYLATE/CAPRATE; COCONUT ALKANES; CYCLOMETHICONE 5; DIMETHICONE; ETHYLHEXYLGLYCERIN; GLYCERIN; GLYCERYL MONOSTEARATE; FERRIC OXIDE RED; LAURETH-7; OCTYLDODECYL NEOPENTANOATE; PEG-100 STEARATE; PHENOXYETHANOL; POLYACRYLAMIDE (1500 MW); POLYHYDROXYSTEARIC ACID (2300 MW); POLYSORBATE 60; STEARIC ACID; TROLAMINE; XANTHAN GUM

Ultra Shade Sunsccreen SPF 30

Active Ingredients Purpose

Titanium Dioxide 5.00% Sunscreen

Zinc Oxid 10.00%

Uses

- Helps prevent sunburn

Keep out of reach of children. If swallowed get help or contact a Poison Control Center right away.

Stop use and ask a doctor if rash occurs

Warnings

Skin Cancer/Skin Aging Alert: Spending time in the sun increases your risk of skin cancer and early skin aging. This product has been shown only to prevent sunburn, not skin cancer or early skin aging.

- For external use only.

- Do not use on damage or broken skin.

- Whenn using this product keep out of eyes. Rinse with water to remove

Directions

- Apply generously 15 minutes before sun exposure
- Reapply:

-after 80 minutes of swimming or sweating

-immediatley after towel drying

- at least every 2 hours

- Chirldren under 6 months of age: ask a doctor

INACTIVE INGREDIENT

Acrylates/C10-30 Alkyl Acrylates Crosspolymer, Alumina, Aqua, Butylene Glycol, C12-15 Alkyl Benzoate, C13-14 Isoparaffin, Cetearyl Alcohol,

Coco-Caprylate/Caprate, Coconut Alkanes, Cyclopentasiloxane, Dimethicone, Ethylhexylglycerin, Glycerin, Glyceryl Stearate, Iron Oxides, Laureth-7, Octoyldodecyl Neopentanoate, Polyhydroxystearic Acid, Triethanolamine, Xanthan Gum

PACKAGE LABEL

TAHERI MD

Ultra Shade Sunscreen SPF 30

Non- Comedogenic

1.7 0z / 50 ml